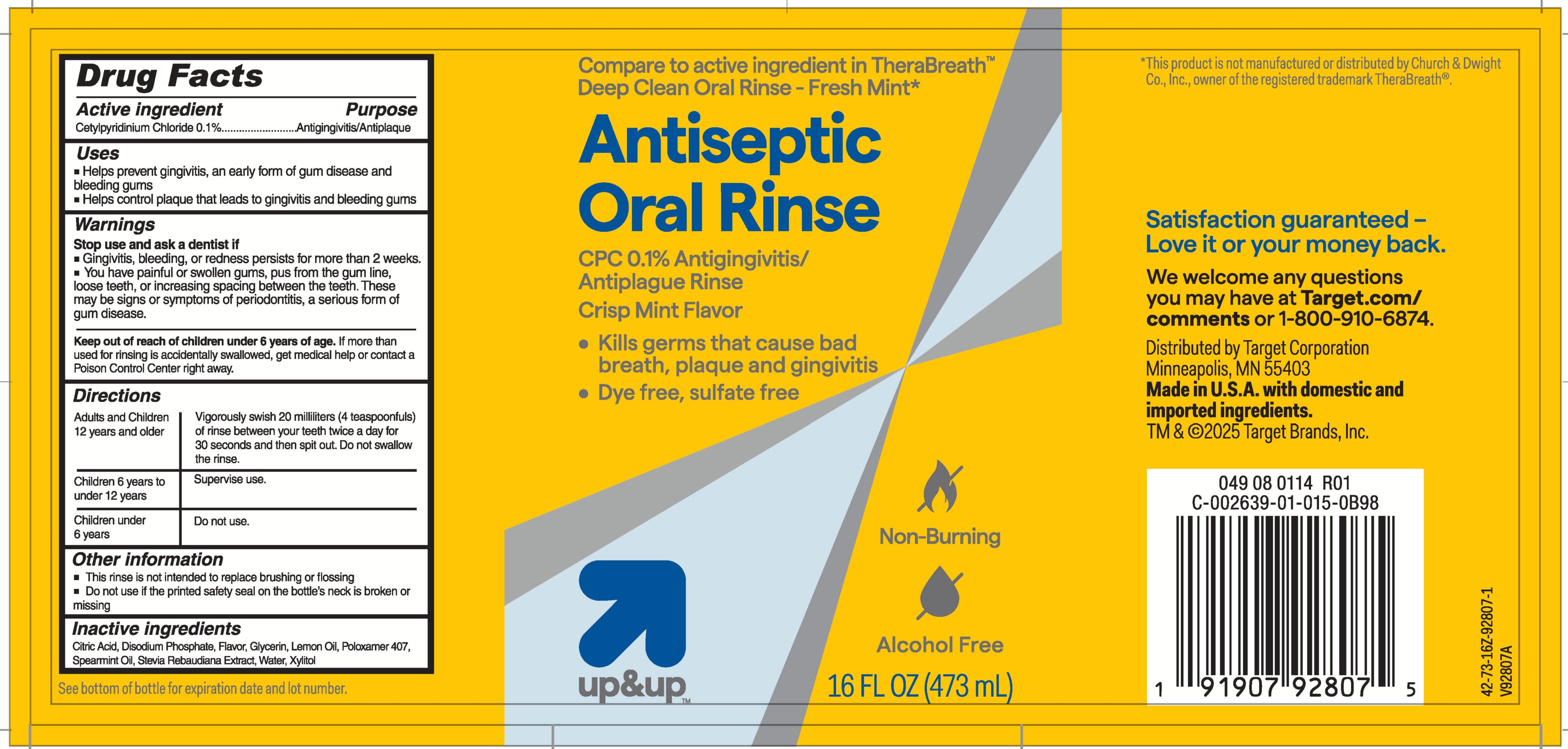 DRUG LABEL: Up and Up Antiseptic
NDC: 82442-807 | Form: RINSE
Manufacturer: Target Corporation
Category: otc | Type: HUMAN OTC DRUG LABEL
Date: 20260119

ACTIVE INGREDIENTS: CETYLPYRIDINIUM CHLORIDE 0.02 g/20 mL
INACTIVE INGREDIENTS: GLYCERIN; STEVIA REBAUDIUNA LEAF; SPEARMINT OIL; LEMON OIL; POLOXAMER 407; WATER; XYLITOL; CITRIC ACID; DISODIUM PHOSPHATE

Up and Up Antiseptic Oral Rinse

Active ingredient

Cetylpyridinium Chloride

Purpose

Antigingivitis/Antiplaque

Uses

- Helps prevent gingivitis, an early form of gum disease and bleeding gums
- Helps control plaque that leads to gingivitis and bleeding gums

Warnings

Stop use and ask a dentist if

- Gingivitis, bleeding, or redness persists for more than 2 weeks.
- You have painful or swollen gums, pus from the gum line, loose teeth, or increasing spacing between the teeth. These may be signs or symptoms of periodontitis, a serious form of gum disease.

Keep out of reach of children under 6 years of age.

If more than used for rinsing is accidently swallowed, get medical help or contact a Poison Control Center right away.

Directions

Adults and Children 12 years and older: Vigorously swish 20 milliters (4 teaspoonfuls) of rinse between your teeth twice a day for 30 seconds and then spit out. Do not swallow the rinse.

Children 6 years to under 12 years: Supervise use.

Children under 6 years: Do not use.

Other information

- This rinse is not intended to replace brushing or flossing
- Do not use if the printed safety seal on the bottle's neck is missing

Inactive ingredients

Citric Acid, Disodium Phosphate, Flavor, Glycerin, Lemon Oil, Poloxamer 407, Spearmint Oil, Stevia Rebaudiana, Water, Xylitol